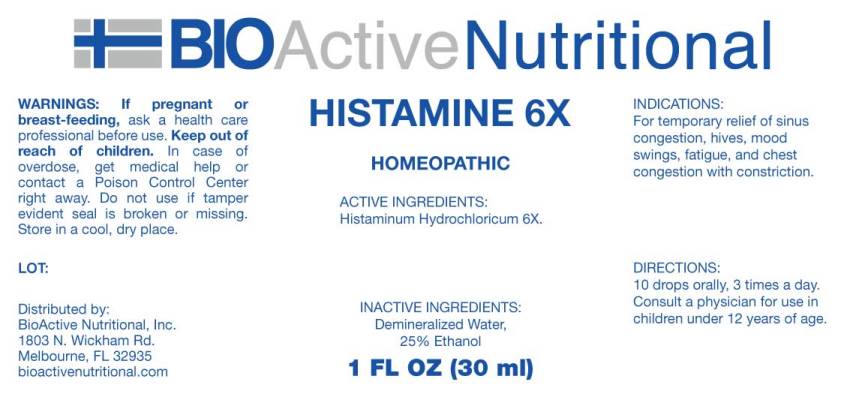 DRUG LABEL: Histamine
NDC: 43857-0309 | Form: LIQUID
Manufacturer: BioActive Nutritional, Inc.
Category: homeopathic | Type: HUMAN OTC DRUG LABEL
Date: 20240830

ACTIVE INGREDIENTS: HISTAMINE DIHYDROCHLORIDE 30 [hp_X]/1 mL
INACTIVE INGREDIENTS: WATER; ALCOHOL

DRUG FACTS:

ACTIVE INGREDIENTS:

Histaminum Hydrochloricum 6X.

PURPOSE:

For temporary relief of sinus congestion, hives, mood swings, fatigue, and chest congestion with constriction.

WARNINGS:

If pregnant or breast-feeding, ask a health care professional before use.

Keep out of reach of children. In case of overdose, get medical help or contact a Poison Control Center right away.

Do not use if tamper evident seal is broken or missing.

Store in cool, dry place.

KEEP OUT OF REACH OF CHILDREN. In case of overdose, get medical help or contact a Poison Control Center right away.

DIRECTIONS:

10 drops orally, 3 times a day. Consult a physician for use in children under 12 years of age.

PURPOSE:

For temporary relief of sinus congestion, hives, mood swings, fatigue, and chest congestion with constriction.

INACTIVE INGREDIENTS:

Demineralized Water, 25% Ethanol

QUESTIONS:

Distributed by:

BioActive Nutritional, Inc.

1803 N. Wickham Rd.

Melbourne, FL 32935

bioactivenutritional.com

PACKAGE LABEL DISPLAY:

BioActive Nutritional

HISTAMINE 6X

HOMEOPATHIC

1 FL OZ (30 ml)